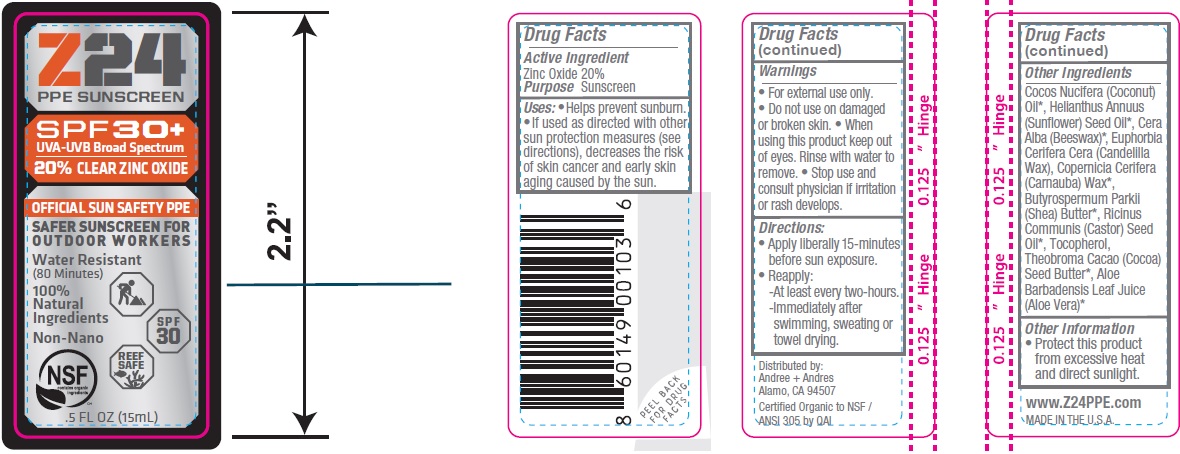 DRUG LABEL: SUNSCREEN
NDC: 62932-189 | Form: OINTMENT
Manufacturer: Private Label Select Ltd CO
Category: otc | Type: HUMAN OTC DRUG LABEL
Date: 20181130

ACTIVE INGREDIENTS: ZINC OXIDE 20 g/100 g
INACTIVE INGREDIENTS: HELIANTHUS ANNUUS SEED WAX; ALOE VERA LEAF; SHEA BUTTER; YELLOW WAX; CANDELILLA WAX; CARNAUBA WAX; CASTOR OIL; COCONUT OIL; TOCOPHEROL; COCOA BUTTER

Z24 PPE Sunscreen SPF30